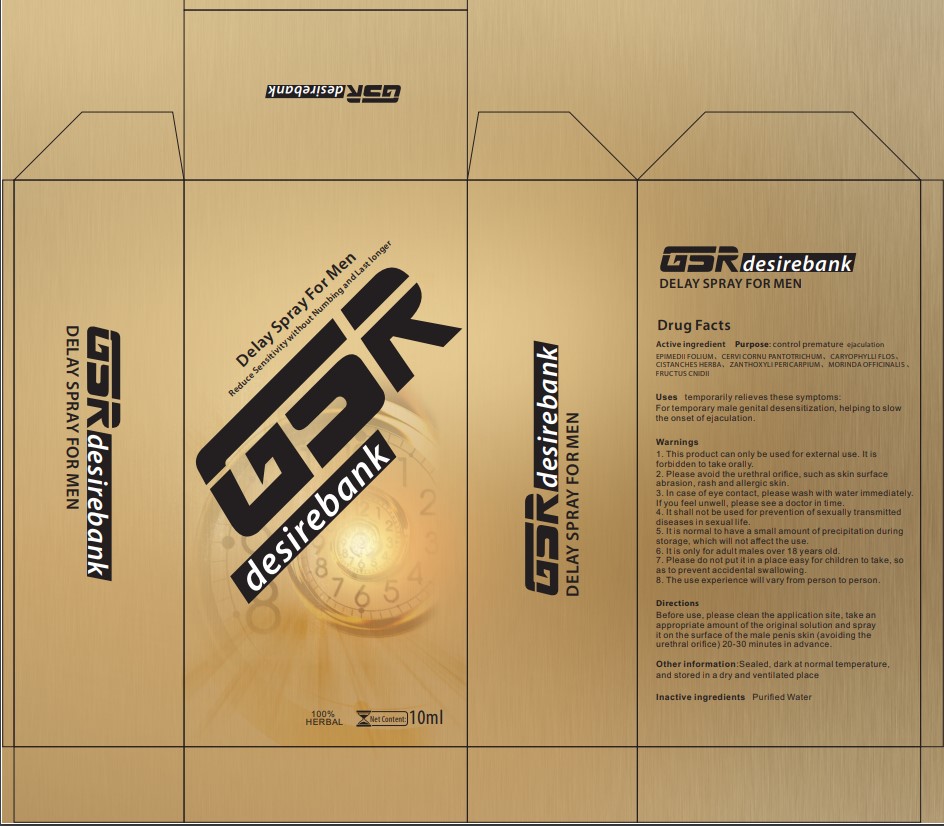 DRUG LABEL: External delayed product  for men
NDC: 83366-001 | Form: LIQUID
Manufacturer: Taizhou Guan Lan Import and Export Co., Ltd
Category: homeopathic | Type: HUMAN OTC DRUG LABEL
Date: 20230328

ACTIVE INGREDIENTS: EPIMEDIUM BREVICORNU WHOLE 5 g/100 g; GYNOCHTHODES OFFICINALIS ROOT 10 g/100 g; CERVUS ELAPHUS HORN 7 g/100 g; CLOVE 6 g/100 g; CISTANCHE DESERTICOLA WHOLE 6 g/100 g; ZANTHOXYLUM BUNGEANUM FRUIT 8 g/100 g; CNIDIUM MONNIERI FRUIT 10 g/100 g
INACTIVE INGREDIENTS: WATER

External delayed spray for men

Active Ingredient

EPIMEDII FOLIUM, CERVI CORNU PANTOTRICHUM, CARYOPHYLLI FLOS,
CISTANCHES HERBA, ZANTHOXYLI PERICARPIUM, MORINDA OFFICINALIS ,
FRUCTUS CNIDII

Purpose

control premature ejaculation

Please place this product in a place that is not easy for children to touch

Please do not put it in a place easy for children to take, so as to prevent accidental swallowing.

Temporarily relieves these symptoms

For temporary male genital desensitization, helping to slow the onset of ejaculation.

Warnings

1. This product can only be used for external use. It is forbidden to take orally.
2. Please avoid the urethral oriﬁce, such as skin surface abrasion, rash and allergic skin.
3. In case of eye contact, please wash with water immediately. If you feel unwell, please see a doctor in time.
4. It shall not be used for prevention of sexually transmitted diseases in sexual life.
5. It is normal to have a small amount of precipitation during storage, which will not aﬀect the use.
6. It is only for adult males over 18 years old.
7. Please do not put it in a place easy for children to take, so as to prevent accidental swallowing.
8. The use experience will vary from person to person.

Directions

Before use, please clean the application site, take an appropriate amount of the original solution and spray it on the surface of the male penis skin (avoiding the urethral oriﬁce) 20-30 minutes in advance.

Other information

Sealed, dark at normal temperature, and stored in a dry and ventilated place

Inactive ingredients

Puriﬁed Water